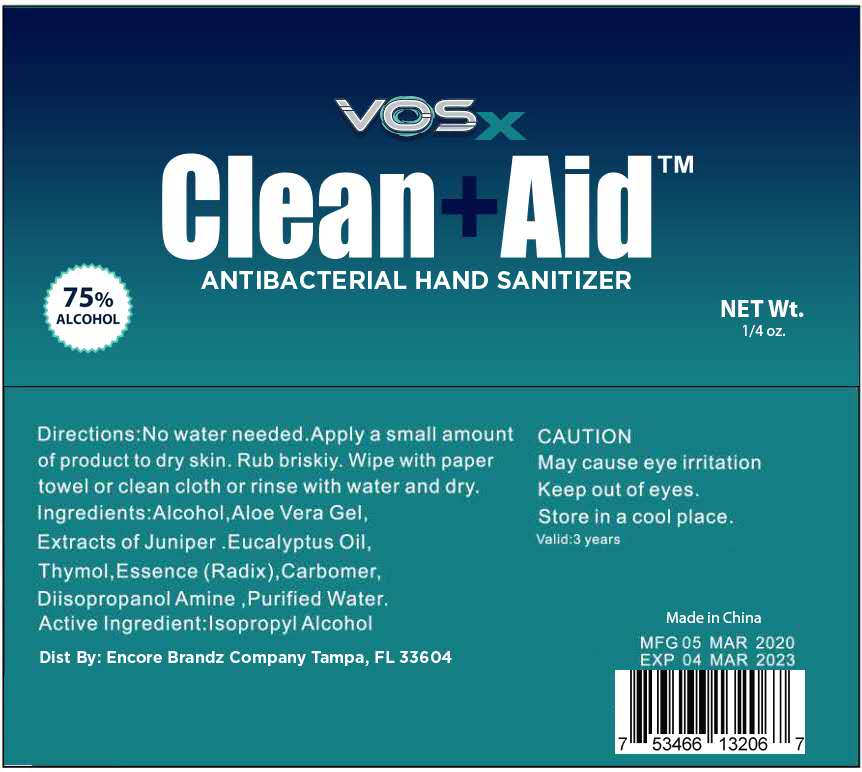 DRUG LABEL: ANTIBACTERIAL HAND SANITIZER
NDC: 74881-007 | Form: GEL
Manufacturer: Huizhou Baozi Biotechnology Co., Ltd.
Category: otc | Type: HUMAN OTC DRUG LABEL
Date: 20200819

ACTIVE INGREDIENTS: ISOPROPYL ALCOHOL 75 mL/100 mL
INACTIVE INGREDIENTS: CARBOMER INTERPOLYMER TYPE A (55000 CPS); WATER; ALOE VERA LEAF; EUCALYPTUS OIL; DIISOPROPANOLAMINE; JUNIPER BERRY; THYMOL; METHYL BENZOATE; ALCOHOL

007 ANTIBACTERIAL HAND SANITIZER

Active Ingredient

Active lngredient:Isopropyl Alcohol

Purpose

/

Uses

No water needed.

Warnings

/

DO NOT USE

/

WHEN USING THIS PRODUCT

/

STOP USE

/

KEEP OUT OF REACH OF CHILDREN

/

Directions

No water needed.Apply a small amount of product to dry skin. Rub briskiy. Wipe with paper towel or clean cloth or rinse with water and dry .

Other information

/

Inactive ingredients

Alcohol ,Aloe Vera GeL,
Extracts of Juniper ,Eucalyptus OiL,
Thymol,Essence (Radix), Carbomer,
Diisopropanol Amine ,Purified Water.